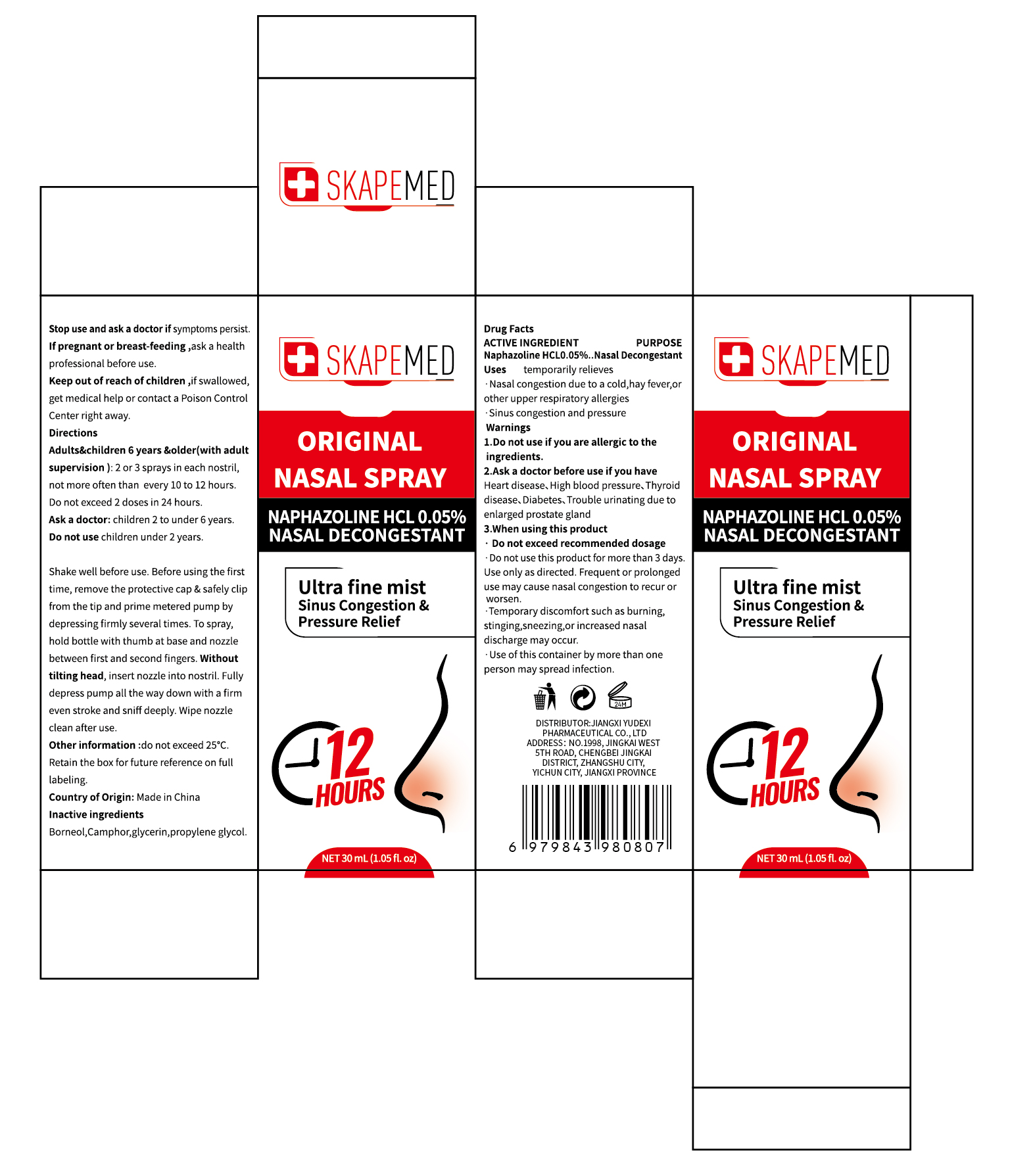 DRUG LABEL: SKAPEMED ORIGINAL NASAL
NDC: 85248-053 | Form: LIQUID
Manufacturer: Jiangxi Yudexi Pharmaceutical Co., LTD
Category: otc | Type: HUMAN OTC DRUG LABEL
Date: 20260205

ACTIVE INGREDIENTS: NAPHAZOLINE HCL 0.05 g/100 mL
INACTIVE INGREDIENTS: CAMPHOR (SYNTHETIC); PROPYLENE GLYCOL; BORNEOL; GLYCERIN

85248-053

Active Ingredient

Naphazoline HCL 0.05%.

Purpose

Nasal Decongestant

Use

temporarily relieves Nasal congestion due to a cold, hay fever, or other upper respiratory allergies ·Sinus congestion and pressure

Warnings

1.Do not use if you are allergic to the ingredients.
2.Ask a doctor before use if you have
Heart disease、High blood pressure、Thyroid disease、Diabetes、Trouble urinating due to
enlarged prostate gland
3.When using this product
·Do not exceed recommended dosage ·Do not use this product for more than 3 days.
Use only as directed. Frequent or prolonged
use may cause nasal congestion to recur or worsen. ·Temporary discomfort such as burning,stinging,sneezing,or increased nasal discharge may occur. ·Use of this container by more than one person may spread infection.

Do not use

children under 2 years.Shake well before use. Before using the first time.remove the protective cap & safely clip from the tip and prime metered pump by depressing firmly several times. To spray, hold bottle with thumb at base and nozzle between first and second fingers. Without tilting head, insert nozzle into nostril. Fully depress pump all the way down with a firm even stroke and sniff deeply. Wipe nozzle clean after use.

When Using

·Do not exceed recommended dosage · Do not use this product for more than 3 days.Use only as directed. Frequent or prolonged use may cause nasal congestion to recur or worsen. ·Temporary discomfort such as burning,stinging,sneezing,or increased nasal discharge may occur.
·Use of this container by more than one person may spread infection.

Stop Use

Stop use and ask a doctor if symptoms persist.

Ask Doctor

children 2 to under 6 years.

Keep Oot Of Reach Of Children

if swallowed,get medical help or contact a Poison Control Center right away

Directions

Adults&children 6 years &older(with adult supervision): 2 or 3 sprays in each nostril, not more often than every 10 to 12 hours.Do not exceed 2 doses in 24 hours

Other information

do not exceed 25°C. Retain the box for future reference on full labeling.

Inactive ingredients

Borneol,Camphor,glycerin,propylene glycol.